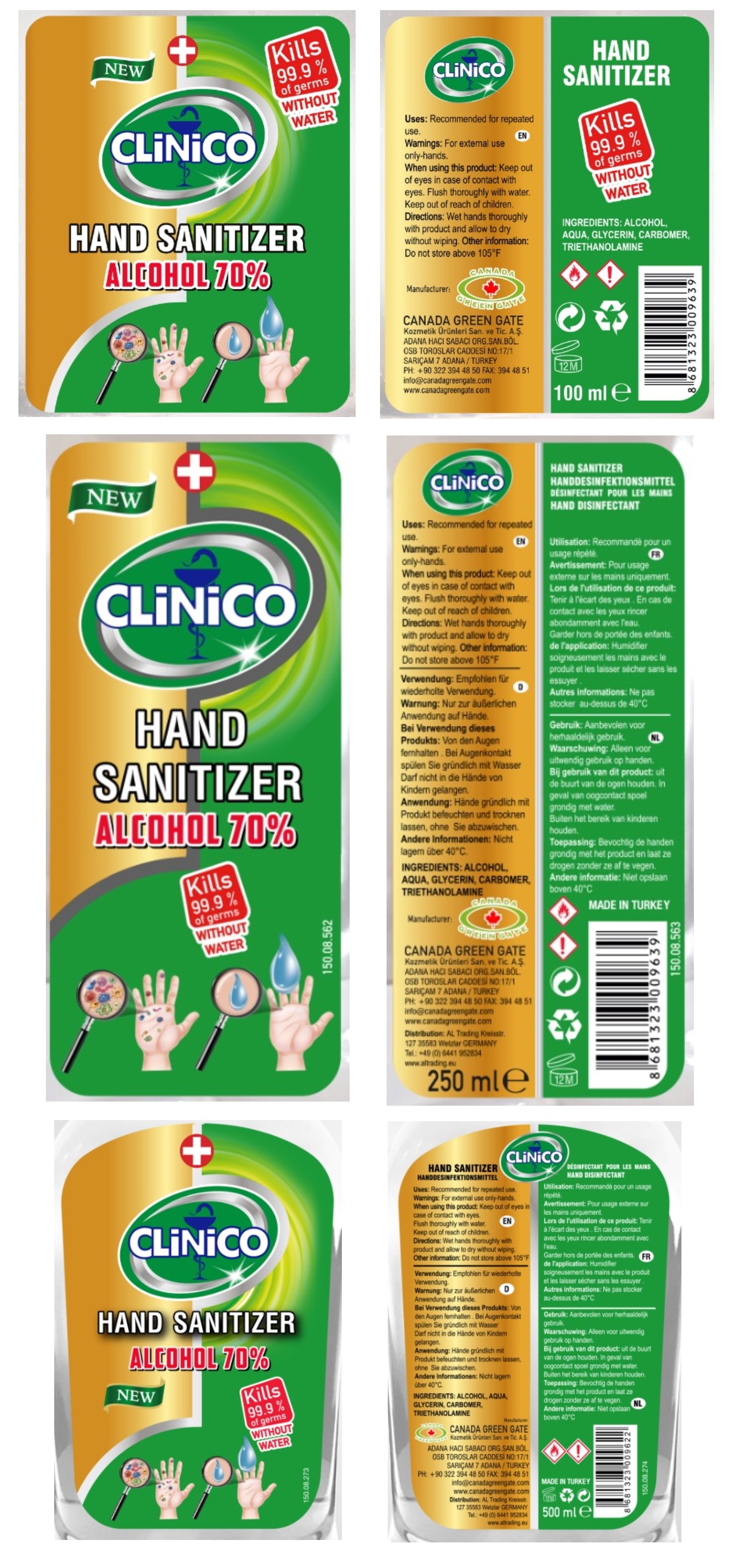 DRUG LABEL: HAND SANITIZER
NDC: 78726-100 | Form: GEL
Manufacturer: CANADA GREEN GATE KOZMETIK URUNLERI SANAYI VE TICARET ANONIM SIRKETI
Category: otc | Type: HUMAN OTC DRUG LABEL
Date: 20200605

ACTIVE INGREDIENTS: ALCOHOL 70 mL/100 mL
INACTIVE INGREDIENTS: WATER; GLYCERIN; CARBOMER HOMOPOLYMER, UNSPECIFIED TYPE; TROLAMINE

CLiNiCO HAND SANITIZER

Active Ingredient:

Alcohol 70%

Purpose:

Antiseptic

INDICATIONS AND USAGE

Uses: Recommended for repeated use.

Warnings: For external use only-hands.

When using this product: Keep out of eyes in case of contact with eyes. Flush thoroughly with water.

Keep out of reach of children.

DOSAGE AND ADMINISTRATION

Directions: Wet hands thoroughly with product and allow to dry without wiping.

Other information: Do not store above 105°F

Inactive Ingredients:

Aqua, Glycerin, Carbomer, Triethanolamine

NEW

Kills 99.9% of germs WITHOUT WATER

Manufacturer:

CANADA GREEN GATE

Kozmetik Ürüneri San. ve Tic. A.S.

ADANA HACI SABACI ORG.SAN.BÖL.

OSB TOROSLAR CADDESI NO:17/1

SARIÇAM 7 ADANA / TURKEY

PH: +90 322 394 48 50 FAX: 394 48 51

info@canadagreengate.com

www.canadagreengate.com

MADE IN TURKEY